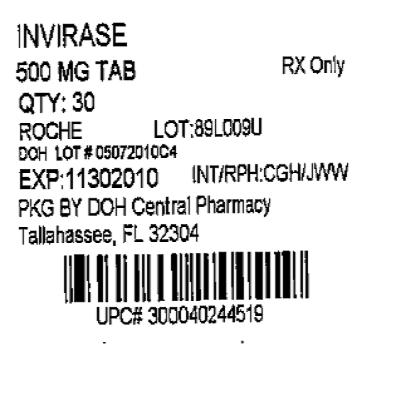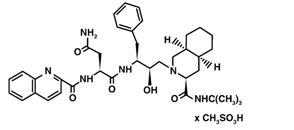 DRUG LABEL: Invirase
NDC: 53808-0674 | Form: TABLET, FILM COATED
Manufacturer: State of Florida DOH Central Pharmacy
Category: prescription | Type: HUMAN PRESCRIPTION DRUG LABEL
Date: 20100920

ACTIVE INGREDIENTS: SAQUINAVIR MESYLATE 500 mg/1 1
INACTIVE INGREDIENTS: LACTOSE; POVIDONE K30; CROSCARMELLOSE SODIUM; MAGNESIUM STEARATE; HYPROMELLOSE; TITANIUM DIOXIDE; TALC; FERRIC OXIDE RED; TRIACETIN

INVIRASE®
(saquinavir mesylate)
CAPSULES and TABLETS

Product identification in this document includes: INVIRASE in reference to saquinavir mesylate; saquinavir soft gel capsules in reference to saquinavir 200 mg soft gel capsule formulation [The term "saquinavir soft gel capsules" used in this label refers to the drug product formerly marketed as "Fortovase" (saquinavir 200 mg soft gel capsule formulation). This formulation has been withdrawn from the market.] , and saquinavir in reference to the active base.

DESCRIPTION

INVIRASE brand of saquinavir mesylate is an inhibitor of the human immunodeficiency virus (HIV) protease. INVIRASE is available as light brown and green, opaque hard gelatin capsules for oral administration in a 200-mg strength (as saquinavir free base). Each capsule also contains the inactive ingredients lactose, microcrystalline cellulose, povidone K30, sodium starch glycolate, talc, and magnesium stearate. Each capsule shell contains gelatin and water with the following dye systems: red iron oxide, yellow iron oxide, black iron oxide, FD&C Blue #2, and titanium dioxide.

INVIRASE is also available as a light orange to greyish- or brownish-orange, oval cylindrical, biconvex film-coated tablet for oral administration in a 500-mg strength (as saquinavir free base). Each tablet also contains the inactive ingredients lactose, microcrystalline cellulose, povidone K30, croscarmellose sodium, and magnesium stearate. Each film coat contains hypromellose, titanium dioxide, talc, iron oxide yellow, iron oxide red, and triacetin.

The chemical name for saquinavir mesylate is N-tert-butyl-decahydro-2-[2(R)-hydroxy-4-phenyl-3(S)-[[N-(2-quinolylcarbonyl)-L-asparaginyl]amino]butyl]-(4aS,8aS)-isoquinoline-3(S)-carboxamide methanesulfonate with a molecular formula C38H50N6O5•CH4O3S and a molecular weight of 766.96. The molecular weight of the free base is 670.86. Saquinavir mesylate has the following structural formula:

Saquinavir mesylate is a white to off-white, very fine powder with an aqueous solubility of 2.22 mg/mL at 25°C.

MICROBIOLOGY

Mechanism of Action

Saquinavir is an inhibitor of HIV protease. HIV protease is an enzyme required for the proteolytic cleavage of viral polyprotein precursors into individual functional proteins found in infectious HIV. Saquinavir is a peptide-like substrate analogue that binds to the protease active site and inhibits the activity of the enzyme. Saquinavir inhibition prevents cleavage of the viral polyproteins resulting in the formation of immature noninfectious virus particles.

Antiviral Activity

In vitro antiviral activity of saquinavir was assessed in lymphoblastoid and monocytic cell lines and in peripheral blood lymphocytes. Saquinavir inhibited HIV activity in both acutely and chronically infected cells. IC50 and IC90 values (50% and 90% inhibitory concentrations) were in the range of 1 to 30 nM and 5 to 80 nM, respectively. In the presence of 40% human serum, the mean IC50 of saquinavir against laboratory strain HIV-1 RF in MT4 cells was 37.7± 5 nM representing a 4-fold increase in the IC50 value. In cell culture, saquinavir demonstrated additive to synergistic effects against HIV-1 in combination with reverse transcriptase inhibitors (didanosine, lamivudine, nevirapine, stavudine and zidovudine) without enhanced cytotoxicity. Saquinavir in combination with the protease inhibitors amprenavir, atazanavir, or lopinavir resulted in synergistic antiviral activity. Saquinavir displayed antiviral activity in vitro against HIV-1 clades A-H (IC50 ranged from 0.9 to 2.5 nM). The IC50 and IC90 values of saquinavir against HIV-2 isolates in vitro ranged from 0.25 nM to 14.6 nM and 4.65 nM to 28.6 nM, respectively.

Drug Resistance

HIV-1 mutants with reduced susceptibility to saquinavir have been selected during in vitro passage. Genotypic analyses of these isolates showed several substitutions in the HIV protease gene. Only the G48V and L90M substitutions were associated with reduced susceptibility to saquinavir, and conferred an increase in the IC50 value of 8- and 3-fold, respectively.

HIV-1 isolates with reduced susceptibility (≥4-fold increase in the IC50 value) to saquinavir emerged in some patients treated with INVIRASE. Genotypic analysis of these isolates identified resistance conferring primary mutations in the protease gene G48V and L90M, and secondary mutations L10I/R/V, I54V/L, A71V/T, G73S, V77I, V82A and I84V that contributed additional resistance to saquinavir. Forty-one isolates from 37 patients failing therapy with INVIRASE had a median decrease in susceptibility to saquinavir of 4.3-fold.

The degree of reduction in in vitro susceptibility to saquinavir of clinical isolates bearing substitutions G48V and L90M depends on the number of secondary mutations present. In general, higher levels of resistance are associated with greater number of mutations only in association with either or both of the primary mutations G48V and L90M. No data are currently available to address the development of resistance in patients receiving saquinavir/ritonavir.

Cross-resistance

Among protease inhibitors, variable cross-resistance has been observed. In one clinical study, 22 HIV-1 isolates with reduced susceptibility (>4-fold increase in the IC50 value) to saquinavir following therapy with INVIRASE were evaluated for cross-resistance to amprenavir, indinavir, nelfinavir and ritonavir. Six of the 22 isolates (27%) remained susceptible to all 4 protease inhibitors, 12 of the 22 isolates (55%) retained susceptibility to at least one of the PIs and 4 out of the 22 isolates (18%) displayed broad cross-resistance to all PIs. Sixteen (73%) and 11 (50%) of the 22 isolates remained susceptible (<4-fold) to amprenavir and indinavir, respectively. Four of 16 (25%) and nine of 21 (43%) with available data remained susceptible to nelfinavir and ritonavir, respectively.

After treatment failure with amprenavir, cross-resistance to saquinavir was evaluated. HIV-1 isolates from 22/22 patients failing treatment with amprenavir and containing one or more mutations M46L/I, I50V, I54L, V32I, I47V, and I84V were susceptible to saquinavir.

CLINICAL PHARMACOLOGY

Pharmacokinetics

The pharmacokinetic properties of INVIRASE have been evaluated in healthy volunteers (n=351) and HIV-infected patients (n=270) after single- and multiple-oral doses of 25, 75, 200, and 600 mg three times daily and in healthy volunteers after intravenous doses of 6, 12, 36 or 72 mg (n=21). The pharmacokinetics of INVIRASE/ritonavir 1000/100 mg twice daily have also been evaluated in HIV-infected patients.

Similar bioavailability was demonstrated when INVIRASE 500 mg film-coated tablet (2 × 500 mg) and INVIRASE 200 mg capsule (5 × 200 mg) were administered with low-dose ritonavir (100 mg) under fed conditions. The ratio of mean exposures (90% confidence intervals) of tablets vs capsules were 1.10 (1.04-1.16) for AUC0-∞ and 1.19 (1.14-1.25) for Cmax.

Absorption and Bioavailability in Adults

Absolute bioavailability of saquinavir administered as INVIRASE averaged 4% (CV 73%, range: 1% to 9%) in 8 healthy volunteers who received a single 600-mg dose (3 × 200 mg) of saquinavir mesylate following a high-fat breakfast (48 g protein, 60 g carbohydrate, 57 g fat; 1006 kcal). The low bioavailability is thought to be due to a combination of incomplete absorption and extensive first-pass metabolism.

INVIRASE in combination with ritonavir at a dose of 1000/100 mg twice daily provides saquinavir systemic exposures over a 24-hour period that are similar to those achieved with saquinavir soft gel capsules (FORTOVASE) with ritonavir 1000/100 mg twice daily and greater than that achieved with saquinavir soft gel capsules 1200 mg three times daily (see Table 1). The 1200 mg three times daily regimen for FORTOVASE was an approved regimen for which efficacy of saquinavir was demonstrated. Thus, the exposure resulting from this FORTOVASE regimen forms the lower bound for efficacy for all subsequent saquinavir dosing regimens.^1

Table 1 Pharmacokinetic Parameters of Saquinavir at Steady-State After Administration of Different Regimens in HIV-Infected Patients
Dosing Regimen | N | AUCτ (ng∙h/mL) | AUC24h (ng∙h/mL) | Cmin (ng/mL)
INVIRASE 600 mg tid (arithmetic mean, %CV) | 10 | 866 (62) | 2598 | 79
Saquinavir soft gel capsules (FORTOVASE) 1200 mg tid (arithmetic mean) | 31 | 7249 | 21747 | 216
INVIRASE 1000 mg bid + ritonavir 100 mg bid (geometric mean and 95% CI) | 24 | 14607 (10218-20882) | 29214 | 371 (245-561)
Saquinavir soft gel capsules 1000 mg bid + ritonavir 100 mg bid (geometric mean and 95% CI) | 24 | 19085 (13943-26124) | 38170 | 433 (301-622)
τ is the dosing interval (ie, 8h if three times daily and 12h if twice daily)

Food Effect

No food effect data are available for INVIRASE in combination with ritonavir.

The mean 24-hour AUC after a single 600-mg oral dose (6 × 100 mg) in healthy volunteers (n=6) was increased from 24 ng∙h/mL (CV 33%), under fasting conditions, to 161 ng∙h/mL (CV 35%) when INVIRASE was given following a high-fat breakfast (48 g protein, 60 g carbohydrate, 57 g fat; 1006 kcal). Saquinavir 24-hour AUC and Cmax (n=6) following the administration of a higher calorie meal (943 kcal, 54 g fat) were on average 2 times higher than after a lower calorie, lower fat meal (355 kcal, 8 g fat). The effect of food has been shown to persist for up to 2 hours.

Saquinavir exposure was similar when saquinavir soft gel capsules plus ritonavir (1000-mg/100-mg twice daily) were administered following a high-fat (45 g fat) or moderate-fat (20 g fat) breakfast.

Distribution in Adults

The mean steady-state volume of distribution following intravenous administration of a 12-mg dose of saquinavir (n=8) was 700 L (CV 39%), suggesting saquinavir partitions into tissues. Saquinavir was approximately 98% bound to plasma proteins over a concentration range of 15 to 700 ng/mL. In 2 patients receiving saquinavir mesylate 600 mg three times daily, cerebrospinal fluid concentrations were negligible when compared to concentrations from matching plasma samples.

Metabolism and Elimination in Adults

In vitro studies using human liver microsomes have shown that the metabolism of saquinavir is cytochrome P450 mediated with the specific isoenzyme, CYP3A4, responsible for more than 90% of the hepatic metabolism. Based on in vitro studies, saquinavir is rapidly metabolized to a range of mono- and di-hydroxylated inactive compounds. In a mass balance study using 600 mg ^14C-saquinavir mesylate (n=8), 88% and 1% of the orally administered radioactivity was recovered in feces and urine, respectively, within 5 days of dosing. In an additional 4 subjects administered 10.5 mg ^14C-saquinavir intravenously, 81% and 3% of the intravenously administered radioactivity was recovered in feces and urine, respectively, within 5 days of dosing. In mass balance studies, 13% of circulating radioactivity in plasma was attributed to unchanged drug after oral administration and the remainder attributed to saquinavir metabolites. Following intravenous administration, 66% of circulating radioactivity was attributed to unchanged drug and the remainder attributed to saquinavir metabolites, suggesting that saquinavir undergoes extensive first-pass metabolism.

Systemic clearance of saquinavir was rapid, 1.14 L/h/kg (CV 12%) after intravenous doses of 6, 36, and 72 mg. The mean residence time of saquinavir was 7 hours (n=8).

Hepatic or Renal Impairment

Saquinavir pharmacokinetics in patients with hepatic or renal impairment has not been investigated (see PRECAUTIONS). Only 1% of saquinavir is excreted in the urine, so the impact of renal impairment on saquinavir elimination should be minimal.

Gender, Race, and Age

A gender difference was observed, with females showing higher saquinavir exposure than males (mean AUC 56% higher, mean Cmax 26% higher), in the relative bioavailability study comparing INVIRASE 500 mg film-coated tablets to the INVIRASE 200 mg capsules in combination with ritonavir. There was no evidence that age and body weight explained the gender difference in this study. A clinically significant difference in safety and efficacy between men and women has not been reported with the approved dosage regimen (saquinavir 1000-mg/ritonavir 100-mg twice daily).

The effect of race on the pharmacokinetics of saquinavir has not been investigated.

Pediatric Patients

The pharmacokinetics of saquinavir have not been sufficiently investigated in pediatric patients.

Geriatric Patients

The pharmacokinetics of saquinavir have not been sufficiently investigated in patients >65 years of age.

Drug Interactions

(see PRECAUTIONS: Drug Interactions)

Drug interaction studies have been completed with INVIRASE and the saquinavir soft gel capsule formulation. Because ritonavir is coadministered, prescribers should refer to the prescribing information for ritonavir regarding drug interactions associated with this drug.

Table 2 summarizes the effect of saquinavir soft gel capsules on the geometric mean AUC and Cmax of coadministered drugs. Table 3 summarizes the effect of coadministered drugs on the geometric mean AUC and Cmax of saquinavir.

Table 2 Effect of Saquinavir on the Pharmacokinetics of Coadministered Drugs
Coadministered Drug | Saquinavir soft gel capsules or saquinavir soft gel capsules/ ritonavir Dose | N | % Change for Coadministered Drug
Coadministered Drug | Saquinavir soft gel capsules or saquinavir soft gel capsules/ ritonavir Dose | N | AUC (95% CI) | Cmax (95% CI)
Clarithromycin 500 mg bid × 7 days | 1200 mg tid × 7 days | 12V
Clarithromycin |  |  | ↑45% (17-81%) | ↑39% (10-76%)
14-OH clarithromycin metabolite |  |  | ↓24% (5-40%) | ↓34% (14-50%)
Enfuvirtide 90 mg SC q12h (bid) for 7 days | 1000/100 mg bid | 12P | ↔ | ↔
Rifabutin 300 mg qd | 1200 mg tid | 14P | ↑44% | ↑45%
Sildenafil 100-mg single dose | 1200 mg tid × 8 days | 27V | ↑210% (150-300%) | ↑140% (80-230%)
Efavirenz 600 mg qd | 1200 mg tid | 13V | ↓12% | ↓13%
 | Invirase or Invirase/ritonavir Dose
Digoxin 0.5 mg single dose | 1000/100 mg bid × 16 days | 16V | ↑49% (32-69%) [90% Confidence Interval] | ↑27% (5-54%)
R-Methadone 60-120 mg qd | 1000/100 mg bid × 14 days | 12M | ↓19% (9-29%) | NA
Ketoconazole 200 mg/day | 1000/100 mg bid | 12V | ↑168% (146-193%) | ↑45% (32-59%)
Midazolam 7.5 mg oral single dose | 1000/100 mg bid | 16V | ↑1144% (975-1339%) | ↑327% (264 -402%)
↑ Denotes an average increase in exposure by the percentage indicated.
↓ Denotes an average decrease in exposure by the percentage indicated.
↔ Denotes no statistically significant change in exposure was observed.
P Patient
V Healthy Volunteers
M Methadone-dependent, HIV negative patients
NA Not Available

Table 3 Effect of Coadministered Drugs on Saquinavir Pharmacokinetics
Coadministered Drug | Saquinavir soft gel capsules Dose | N | % Change for Saquinavir
Coadministered Drug | Saquinavir soft gel capsules Dose | N | AUC (95% CI) | Cmax (95% CI)
Clarithromycin 500 mg bid × 7 days | 1200 mg tid × 7 days | 12V | ↑177% (108-269%) | ↑187% (105-300%)
Efavirenz 600 mg qd | 1200 mg tid | 13V | ↓62% | ↓50%
Indinavir 800 mg q8h × 2 days | 1200 mg single dose | 6V | ↑364% (190-644%) | ↑299% (138-568%)
Rifabutin 300 mg qd | 1200 mg tid | 14P | ↓47% | ↓39%
Ritonavir 400 mg bid × 14 days | 400 mg bid × 14 days [Compared to standard saquinavir soft gel capsules 1200 mg tid regimen (n=33).] | 8V | ↑121% (7-359%) | ↑64% [Did not reach statistical significance.]
Lopinavir/ritonavir
Evidence from several clinical trials indicates that saquinavir concentrations achieved with saquinavir 1000 mg + lopinavir/ritonavir 400/100 mg BID are similar to those achieved following saquinavir/ritonavir 1000/100 mg BID.
Coadministered Drug | Invirase or Invirase/ritonavir Dose | N | % Change for Saquinavir
Coadministered Drug | Invirase or Invirase/ritonavir Dose | N | AUC (95% CI) | Cmax (95% CI)
Atazanavir 300 mg qd | 1600/100 mg qd | 18P | ↑60% (16-122%) | ↑42% (10-84%)
Fosamprenavir 700 mg bid | 1000 mg bid/100 mg bid | 18P | ↓15% (-33% to 9%) | ↔
Ritonavir 100 mg bid | 1000 mg bid [Compared to standard INVIRASE 600 mg tid regimen (n=114).] | 24P | ↑1124% | ↑1325%
Tenofovir 300 mg qd | 1000 mg bid/100 mg bid | 18P | ↔ | ↔
Tipranavir 500 mg + ritonavir 200 mg bid | 600 mg bid/100 mg bid | 20P | ↓76% (68-81%) [90% Confidence Interval] | ↓70% (60-77%)
Omeprazole 40 mg qd × 5 days | 1000/100 mg bid × 15 days | 19V | ↑82% (37-234%) | ↑ 75% (31-234%)
Ketoconazole 200 mg/day | 1000 mg bid/100 mg bid | 20V | ↔ | ↔
↑ Denotes an average increase in exposure by the percentage indicated.
↓ Denotes an average decrease in exposure by the percentage indicated.
↔ Mean change <10%
P Patient
V Healthy Volunteers

For information regarding clinical recommendations, see PRECAUTIONS: Drug Interactions, Table 5.

INDICATIONS AND USAGE

INVIRASE in combination with ritonavir and other antiretroviral agents is indicated for the treatment of HIV infection. The twice daily administration of INVIRASE in combination with ritonavir is supported by safety data from the MaxCmin 1 study (see Table 6) and pharmacokinetic data (see Table 1). The efficacy of INVIRASE with ritonavir has not been compared against the efficacy of antiretroviral regimens currently considered standard of care.

Description of Clinical Studies

In a randomized, double-blind clinical study (NV14256) in zidovudine-experienced, HIV-infected patients, INVIRASE in combination with zalcitabine was shown to be superior to either INVIRASE or zalcitabine monotherapy in decreasing the cumulative incidence of clinical disease progression to AIDS-defining events or death. Furthermore, in a randomized study (ACTG229/NV14255), patients with advanced HIV infection with history of prolonged zidovudine treatment and who were given INVIRASE 600 mg (three times daily) + zidovudine + zalcitabine experienced greater increases in CD4 cell counts as compared to those who received INVIRASE + zidovudine or zalcitabine + zidovudine. It should be noted that HIV treatment regimens that were used in these initial clinical studies of INVIRASE are no longer considered standard of care.

Saquinavir gel capsule 1000 mg twice daily coadministered with ritonavir 100 mg twice daily was studied in a heterogeneous population of 148 HIV-infected patients (MaxCmin 1 study). At baseline 42 were treatment naïve and 106 were treatment experienced (of which 52 had an HIV RNA level <400 copies/mL at baseline). Results showed that 91/148 (61%) subjects achieved and/or sustained an HIV RNA level <400 copies/mL at the completion of 48 weeks.

CONTRAINDICATIONS

INVIRASE is contraindicated in patients with clinically significant hypersensitivity (e.g. anaphylactic reaction, Stevens-Johnson syndrome) to saquinavir, saquinavir mesylate, or any of its ingredients including ritonavir.

INVIRASE/ritonavir should not be administered concurrently with rifampin, terfenadine, cisapride, astemizole, pimozide, triazolam, midazolam or ergot derivatives. Inhibition of CYP3A4 by saquinavir and ritonavir could result in elevated plasma concentrations of these drugs, potentially causing serious or life-threatening reactions, such as cardiac arrhythmias or prolonged sedation (see PRECAUTIONS: Drug Interactions).

INVIRASE/ritonavir should not be given together with rifampin, due to the risk of severe hepatocellular toxicity if the three drugs are given together (see PRECAUTIONS: Drug Interactions).

INVIRASE when administered with ritonavir is contraindicated in patients with severe hepatic impairment.

INVIRASE/ritonavir should not be administered concurrently with drugs listed in Table 4.

Table 4 Drugs That Are Contraindicated With INVIRASE/Ritonavir
Drug Class | Drugs Within Class That Are Contraindicated With INVIRASE | Clinical Comment
Antiarrhythmics | Amiodarone, bepridil, flecainide, propafenone, quinidine | Potential for serious and/or threatening reactions.
Ergot Derivatives | Dihydroergotamine, ergonovine, ergotamine, methylergonovine | Potential for serious and life threatening reactions such as ergot toxicity characterized by peripheral vasospasm and ischemia of the extremities and other tissues.
Antimycobacterial Agents | Rifampin | Rifampin should not be administered in patients taking ritonavir-boosted INVIRASE part of an ART regimen due to the risk of severe hepatocellular toxicity.
GI Motility Agent | Cisapride | Potential for serious and/or life threatening reactions such as cardiac arrhythmias.
Neuroleptics | Pimozide | Potential for serious and/or life threatening reactions such as cardiac arrhythmias.
Sedative/Hypnotics | Triazolam, orally administered midazolam | Potential for serious and/or life threatening reactions such as prolonged or increased sedation or respiratory depression. Triazolam and orally administered midazolam are extensively metabolized by CYP3A4. Coadministration of triazolam and orally administered midazolam with INVIRASE/ritonavir may cause large increases in the concentration of these benzodiazepines.
HMG-CoA Reductase Inhibitors | Lovastatin, Simvastatin | Potential for myopathy including rhabdomyolysis.

WARNINGS

INVIRASE must be used in combination with ritonavir.

Interaction with HMG-CoA Reductase Inhibitors

INVIRASE should not be used with lovastatin or simvastatin (see CONTRAINDICATIONS). Caution should be exercised if HIV protease inhibitors, including INVIRASE, are used concurrently with other HMG-CoA reductase inhibitors that are also metabolized by the CYP3A4 pathway (eg, atorvastatin). Since increased concentrations of statins can, in rare cases, cause severe adverse events such as myopathy including rhabdomyolysis, this risk may be increased when HIV protease inhibitors, including saquinavir, are used in combination with these drugs (see PRECAUTIONS: Drug Interactions).

Interaction with St. John's Wort (hypericum perforatum)

Concomitant use of INVIRASE and St. John's wort (hypericum perforatum) or products containing St. John's wort is not recommended. Coadministration of protease inhibitors, including INVIRASE, with St. John's wort is expected to substantially decrease protease-inhibitor concentrations and may result in sub-optimal levels of INVIRASE and lead to loss of virologic response and possible resistance to INVIRASE or to the class of protease inhibitors (see PRECAUTIONS: Drug Interactions).

Interaction with Digoxin

Caution should be exercised when INVIRASE and digoxin are coadministered; serum concentration of digoxin should be monitored and the dose of digoxin may need to be reduced (see PRECAUTIONS: Drug Interactions).

Interaction with Fluticasone

A drug interaction study in healthy subjects has shown that ritonavir significantly increases plasma fluticasone propionate exposures, resulting in significantly decreased serum cortisol concentrations. Concomitant use of INVIRASE with ritonavir and fluticasone propionate is expected to produce the same effects. Systemic corticosteroid effects including Cushing's syndrome and adrenal suppression have been reported during postmarketing use in patients receiving ritonavir and inhaled or intranasally administered fluticasone propionate. Therefore, coadministration of fluticasone propionate and INVIRASE/ritonavir is not recommended unless the potential benefit to the patient outweighs the risk of systemic corticosteroid side effects (see PRECAUTIONS: Drug Interactions).

Diabetes Mellitus and Hyperglycemia

New onset diabetes mellitus, exacerbation of preexisting diabetes mellitus and hyperglycemia have been reported during postmarketing surveillance in HIV-infected patients receiving protease-inhibitor therapy. Some patients required either initiation or dose adjustments of insulin or oral hypoglycemic agents for the treatment of these events. In some cases diabetic ketoacidosis has occurred. In those patients who discontinued protease-inhibitor therapy, hyperglycemia persisted in some cases. Because these events have been reported voluntarily during clinical practice, estimates of frequency cannot be made and a causal relationship between protease-inhibitor therapy and these events has not been established.

PRECAUTIONS

General

If a serious or severe toxicity occurs during treatment with INVIRASE, INVIRASE should be interrupted until the etiology of the event is identified or the toxicity resolves. At that time, resumption of treatment with full-dose INVIRASE may be considered. For antiretroviral agents used in combination with INVIRASE, physicians should refer to the complete product information for these drugs for dose adjustment recommendations and for information regarding drug-associated adverse reactions.

Hepatic Effects

The use of INVIRASE (in combination with ritonavir) by patients with hepatic impairment has not been studied. In the absence of such studies, caution should be exercised, as increases in saquinavir levels and/or increases in liver enzymes may occur. In patients with underlying hepatitis B or C, cirrhosis, chronic alcoholism and/or other underlying liver abnormalities there have been reports of worsening liver disease.

Renal Effects

Renal clearance is only a minor elimination pathway; the principal route of metabolism and excretion for saquinavir is by the liver. Therefore, no initial dose adjustment is necessary for patients with renal impairment. However, patients with severe renal impairment have not been studied, and caution should be exercised when prescribing saquinavir in this population.

Hemophilia

There have been reports of spontaneous bleeding in patients with hemophilia A and B treated with protease inhibitors. In some patients additional factor VIII was required. In the majority of reported cases treatment with protease inhibitors was continued or restarted. A causal relationship between protease inhibitor therapy and these episodes has not been established.

Hyperlipidemia

Elevated cholesterol and/or triglyceride levels have been observed in some patients taking saquinavir in combination with ritonavir. Marked elevation in triglyceride levels is a risk factor for development of pancreatitis. Cholesterol and triglyceride levels should be monitored prior to initiating combination dosing regimen of INVIRASE with ritonavir, and at periodic intervals while on such therapy. In these patients, lipid disorders should be managed as clinically appropriate.

Lactose Intolerance

Each capsule contains lactose (anhydrous) 63.3 mg. This quantity should not induce specific symptoms of intolerance.

Fat Redistribution

Redistribution/accumulation of body fat including central obesity, dorsocervical fat enlargement (buffalo hump), facial wasting, peripheral wasting, breast enlargement, and "cushingoid appearance" have been observed in patients receiving antiretroviral therapy. A causal relationship between protease-inhibitor therapy and these events has not been established and the long-term consequences are currently unknown.

Immune reconstitution syndrome has been reported in patients treated with combination antiretroviral therapy, including INVIRASE. During the initial phase of combination antiretroviral treatment, patients whose immune system responds may develop an inflammatory response to indolent or residual opportunistic infections (such as Mycobacterium avium infection, cytomegalovirus, Pneumocystis jiroveci pneumonia [PCP], or tuberculosis), which may necessitate further evaluation and treatment.

Resistance/Cross-resistance

Varying degrees of cross-resistance among protease inhibitors have been observed. Continued administration of INVIRASE therapy following loss of viral suppression may increase the likelihood of cross-resistance to other protease inhibitors (see MICROBIOLOGY).

Information for Patients

A statement to patients and health care providers is included on the product's bottle label: ALERT: Find out about medicines that should NOT be taken with INVIRASE.

INVIRASE may interact with some drugs; therefore, patients should be advised to report to their doctor the use of any other prescription, nonprescription medication, or herbal products, particularly St. John's wort.

Patients should be informed that INVIRASE is not a cure for HIV infection and that they may continue to acquire illnesses associated with advanced HIV infection, including opportunistic infections. Patients should be advised that INVIRASE must be used in combination with ritonavir, which significantly inhibits saquinavir's metabolism to provide increased plasma saquinavir levels.

Patients should be informed that redistribution or accumulation of body fat may occur in patients receiving protease inhibitors and that the cause and long-term health effects of these conditions are not known at this time.

Patients should be told that the long-term effects of INVIRASE are unknown at this time. They should be informed that INVIRASE therapy has not been shown to reduce the risk of transmitting HIV to others through sexual contact or blood contamination.

Patients should be advised that INVIRASE administered with ritonavir should be taken within 2 hours after a full meal (see CLINICAL PHARMACOLOGY: Pharmacokinetics). When INVIRASE is taken without food, concentrations of saquinavir in the blood are substantially reduced and may result in no antiviral activity. Patients should be advised of the importance of taking their medication every day, as prescribed, to achieve maximum benefit. Patients should not alter the dose or discontinue therapy without consulting their physician. If a dose is missed, patients should take the next dose as soon as possible. However, the patient should not double the next dose.

Laboratory Tests

Clinical chemistry tests, viral load, and CD4 count should be performed prior to initiating INVIRASE therapy and at appropriate intervals thereafter. Elevated nonfasting triglyceride levels have been observed in patients in saquinavir trials. Triglyceride levels should be periodically monitored during therapy. For comprehensive information concerning laboratory test alterations associated with use of other antiretroviral therapies, physicians should refer to the complete product information for these drugs.

Drug Interactions

Drug interaction studies have been completed with INVIRASE and saquinavir soft gel capsules. Observations from drug interaction studies with saquinavir soft gel capsules may not be predictive for INVIRASE/ritonavir. Because ritonavir is coadministered, prescribers should also refer to the prescribing information for ritonavir regarding drug interactions associated with this agent.

The metabolism of saquinavir is mediated by cytochrome P450, with the specific isoenzyme CYP3A4 responsible for 90% of the hepatic metabolism. Additionally, saquinavir is a substrate for P-Glycoprotein (Pgp). Therefore, drugs that affect CYP3A4 and/or Pgp, may modify the pharmacokinetics of saquinavir. Similarly, saquinavir might also modify the pharmacokinetics of other drugs that are substrates for CYP3A4 or Pgp.

Drugs that are contraindicated specifically due to the expected magnitude of interaction and potential for serious adverse events are listed in Table 4 under CONTRAINDICATIONS. These recommendations are based on either drug interaction studies or predicted interactions due to the expected magnitude of interaction and potential for serious events or loss of efficacy.

Drug interactions that have been established based on drug interaction studies are listed with the pharmacokinetic results in Table 2, which summarizes the effect of saquinavir, administered as saquinavir soft gel capsules or INVIRASE, on the geometric mean AUC and Cmax of coadministered drugs and Table 3, which summarizes the effect of coadministered drugs on the geometric mean AUC and Cmax of saquinavir. Clinical dose recommendations can be found in Table 5. The magnitude of the interactions may be different when INVIRASE is given with ritonavir (see CLINICAL PHARMACOLOGY).

When coadministering INVIRASE/ritonavir with any agent having a narrow therapeutic margin, such as anticoagulants, anticonvulsants, and antiarrhythmics, special attention is warranted. With some agents, the metabolism may be induced, resulting in decreased concentrations. Examples and clinical dose recommendations can be found in Table 5.

Table 5 Established and Other Potentially Significant Drug Interactions: Alteration in Dose or Regimen May Be Recommended Based on Drug Interaction Studies or on Predicted Interaction with INVIRASE/ritonavir
Concomitant Drug Class: Drug Name | Effect on Concentration of Saquinavir or Concomitant Drug | Clinical Comment
HIV-Antiviral Agents
Non-nucleoside reverse transcriptase inhibitor: Delavirdine [INVIRASE/ritonavir interaction has not been evaluated.] | ↑ Saquinavir Effect on delavirdine is not well established | Appropriate doses of the combination with respect to safety and efficacy have not been established.
Non-nucleoside reverse transcriptase inhibitor: Efavirenz [See CLINICAL PHARMACOLOGY: Pharmacokinetics, Table 2 and Table 3 for magnitude of interactions.] , nevirapine | ↓ Saquinavir ↔ Efavirenz | Appropriate doses of the combination of efavirenz or nevirapine and INVIRASE/ritonavir (1000/100 mg bid) with respect to safety and efficacy have not been established.
HIV protease inhibitor: Atazanavir | INVIRASE/ritonavir ↑ Saquinavir ↑ Ritonavir ↔ Atazanavir | Appropriate dosing recommendations for this combination, with respect to efficacy and safety, have not been established. When 1600 mg INVIRASE/100 mg ritonavir and 300 mg atazanavir were coadministered, plasma concentrations of saquinavir and ritonavir were increased.
HIV protease inhibitor: Indinavir | ↑ Saquinavir Effect on indinavir is not well established | Appropriate doses of the combination of indinavir and INVIRASE/ritonavir with respect to safety and efficacy have not been established.
HIV protease inhibitor: Lopinavir/ritonavir (coformulated capsule) | ↔ Saquinavir ↔ Lopinavir ↓ Ritonavir | Evidence from several clinical trials indicates that saquinavir concentrations achieved with the saquinavir and lopinavir/ritonavir combination are similar to those achieved following saquinavir/ritonavir 1000/100 mg. The recommended dose for this combination is saquinavir 1000 mg plus lopinavir/ritonavir 400/100 mg bid.
HIV protease inhibitor: Tipranavir/ritonavir | ↓ Saquinavir | Combining saquinavir with tipranavir/ritonavir is not recommended.
HIV fusion inhibitor: Enfuvirtide | Saquinavir soft gel capsules/ritonavir ↔ enfuvirtide | No clinically significant interaction was noted from a study in 12 HIV patients who received enfuvirtide concomitantly with saquinavir soft gel capsules/ritonavir 1000/100 mg bid. No dose adjustments are required.
Other Agents
Antiarrhythmics: Lidocaine (systemic) | ↑ Antiarrhythmics | Caution is warranted and therapeutic concentration monitoring, if available, is recommended for antiarrhythmics given with INVIRASE/ritonavir.
Anticoagulant: Warfarin | ↑ Warfarin | Concentrations of warfarin may be affected. It is recommended that INR (international normalized ratio) be monitored.
Anticonvulsants: Carbamazepine, phenobarbital, phenytoin | ↓ Saquinavir Effect on carbamazepine, phenobarbital, and phenytoin is not well established | Use with caution, saquinavir may be less effective due to decreased saquinavir plasma concentrations in patients taking these agents concomitantly.
Anti-infective: Clarithromycin | ↑ Saquinavir ↑ Clarithromycin | Appropriate doses of the combination of clarithromycin and INVIRASE/ritonavir with respect to safety and efficacy have not been established. Due to the known effect of ritonavir on clarithromycin concentrations, the following dose adjustments are recommended: For patients with renal impairment, the following dosage adjustments should be considered:; - For patients with CLCR 30 to 60 mL/min the dose of clarithromycin should be reduced by 50%. - For patients with CLCR <30 mL/min the dose of clarithromycin should be decreased by 75%.; No dose adjustment for patients with normal renal function is necessary.
Antifungal: Ketoconazole, itraconazole | ↔ Saquinavir ↔ Ritonavir ↑ Ketoconazole | Appropriate doses of the combination of ketoconazole or itraconazole and INVIRASE/ritonavir with respect to safety and efficacy have not been established. When INVIRASE/ritonavir and ketoconazole are coadministered, plasma concentration of ketoconazole was increased (see Table 2). Hence, doses of ketoconazole > 200 mg/day are not recommended.
Antimycobacterial: Rifabutin | ↓ Saquinavir ↑ Rifabutin | Appropriate doses of the combination of rifabutin and INVIRASE/ritonavir with respect to safety and efficacy have not been established.
Benzodiazepines: Alprazolam, clorazepate, diazepam, flurazepam | ↑ Benzodiazepines | Clinical significance is unknown; however, a decrease in benzodiazepine dose may be needed.
Benzodiazepine: Intravenously administered Midazolam | ↑ Midazolam | Midazolam is extensively metabolized by CYP3A4. Increases in the concentration of midazolam are expected to be significantly higher with oral than parenteral administration. Therefore, INVIRASE should not be given with orally administered midazolam [see Contraindications (4)]. If INVIRASE is coadministered with parenteral midazolam, close clinical monitoring for respiratory depression and/or prolonged sedation should be exercised and dosage adjustment should be considered.
Calcium channel blockers: Diltiazem, felodipine, nifedipine, nicardipine, nimodipine, verapamil, amlodipine, nisoldipine, isradipine | ↑ Calcium channel blockers | Caution is warranted and clinical monitoring of patients is recommended.
Corticosteroid: Dexamethasone | ↓ Saquinavir | Use with caution, saquinavir may be less effective due to decreased saquinavir plasma concentrations in patients taking these agents concomitantly.
Digitalis Glycosides: Digoxin | ↑ Digoxin Increases in serum digoxin concentration were greater in female subjects as compared to male subjects when digoxin was coadministered with INVIRASE/ritonavir. | Concomitant use of INVIRASE/ritonavir with digoxin results in a significant increase in serum concentrations of digoxin. Caution should be exercised when INVIRASE/ritonavir and digoxin are coadministered; serum digoxin concentrations should be monitored and the dose of digoxin may need to be reduced when coadministered with INVIRASE/ritonavir (see WARNINGS).
Inhaled/nasal steroid: Fluticasone | INVIRASE/ritonavir ↑ Fluticasone | Concomitant use of fluticasone propionate and INVIRASE/ritonavir may increase plasma concentrations of fluticasone propionate, resulting in significantly reduced serum cortisol concentrations. Coadministration of fluticasone propionate and INVIRASE/ritonavir is not recommended unless the potential benefit to the patient outweighs the risk of systemic corticosteroid side effects (see WARNINGS).
HMG-CoA reductase inhibitors: Atorvastatin, rosuvastatin | ↑ Atorvastatin ↑ Rosuvastatin | Use lowest possible dose of atorvastatin or rosuvastatin with careful monitoring, or consider other HMG-CoA reductase inhibitors such as fluvastatin in combination with Invirase/ritonavir (see WARNINGS).
Immunosuppressants: Cyclosporine, tacrolimus, rapamycin | ↑ Immunosuppressants | Therapeutic concentration monitoring is recommended for immunosuppressant agents when coadministered with INVIRASE/ritonavir.
Narcotic analgesic: Methadone | ↓ Methadone | Dosage of methadone may need to be increased when coadministered with INVIRASE/ritonavir.
Oral contraceptives: Ethinyl estradiol | ↓ Ethinyl estradiol | Alternative or additional contraceptive measures should be used when estrogen-based oral contraceptives and INVIRASE/ritonavir are coadministered.
PDE5 inhibitors (phosphodiesterase type 5 inhibitors): Sildenafil, vardenafil, tadalafil | ↑ Sildenafil ↔ Saquinavir ↑ Vardenafil ↑ Tadalafil | Use sildenafil with caution at reduced doses of 25 mg every 48 hours with increased monitoring of adverse events when administered concomitantly with INVIRASE/ritonavir. Use vardenafil with caution at reduced doses of no more than 2.5 mg every 72 hours with increased monitoring of adverse events when administered concomitantly with INVIRASE/ritonavir. Use tadalafil with caution at reduced doses of no more than 10 mg every 72 hours with increased monitoring of adverse events when administered concomitantly with INVIRASE/ritonavir.
Antidepressant: Trazodone | ↑ Trazodone | Concomitant use of trazodone and INVIRASE/ritonavir may increase plasma concentration of trazodone. Adverse events of nausea, dizziness, hypotension and syncope have been observed following coadministration of trazodone and ritonavir. If trazodone is used with a CYP3A4 inhibitor such as INVIRASE/ritonavir, the combination should be used with caution and lower dose of trazodone should be considered.
Tricyclic antidepressants: Amitriptyline, imipramine | ↑ Tricyclics | Therapeutic concentration monitoring is recommended for tricyclic antidepressants when coadministered with INVIRASE/ritonavir.
Proton pump inhibitors: Omeprazole | ↑ Saquinavir | When INVIRASE/ritonavir is co-administered with omeprazole, saquinavir concentrations are increased significantly. If omeprazole or another proton pump inhibitor is taken concomitantly with INVIRASE/ritonavir, caution is advised and monitoring for potential saquinavir toxicities is recommended, particularly gastrointestinal symptoms, increased triglycerides, and deep vein thrombosis.
Herbal Products: St. John's wort (hypericum perforatum) | ↓ Saquinavir | Coadministration may lead to loss of virologic response and possible resistance to INVIRASE or to the class of protease inhibitors (see WARNINGS).
Garlic Capsules | ↓ Saquinavir | Coadministration of garlic capsules and saquinavir is not recommended due to the potential for garlic capsules to induce the metabolism of saquinavir which may result in sub-therapeutic saquinavir concentrations.

Drugs That Are Mainly Metabolized by CYP3A4

Although specific studies have not been performed, coadministration with drugs that are mainly metabolized by CYP3A4 (e.g., calcium channel blockers, dapsone, disopyramide, quinine, amiodarone, quinidine, warfarin, tacrolimus, cyclosporine, ergot derivatives, pimozide, carbamazepine, fentanyl, alfentanyl, alprazolam, and triazolam) may result in elevated plasma concentrations of these drugs when coadministered with saquinavir; therefore, these combinations should be used with caution. Since INVIRASE is coadministered with ritonavir, the ritonavir label should be reviewed for additional drugs that should not be coadministered.

Inducers of CYP3A4

Coadministration with compounds that are potent inducers of CYP3A4 (e.g., phenobarbital, phenytoin, dexamethasone, carbamazepine) may result in decreased plasma levels of saquinavir.

Carcinogenesis

Carcinogenicity studies found no indication of carcinogenic activity in rats and mice administered saquinavir for approximately 2 years. Because of limited bioavailability of saquinavir in animals, the plasma exposures (AUC values) in the respective species were approximately 29% (using rat) and 65% (using mouse) of those obtained in humans at the recommended clinical dose boosted with ritonavir.

Mutagenesis

Mutagenicity and genotoxicity studies, with and without metabolic activation where appropriate, have shown that saquinavir has no mutagenic activity in vitro in either bacterial (Ames test) or mammalian cells (Chinese hamster lung V79/HPRT test). Saquinavir does not induce chromosomal damage in vivo in the mouse micronucleus assay or in vitro in human peripheral blood lymphocytes, and does not induce primary DNA damage in vitro in the unscheduled DNA synthesis test.

Impairment of Fertility

No adverse effects were reported in fertility and reproductive performance study conducted in rats. Because of limited bioavailability of saquinavir in animals, the maximal plasma exposures achieved in rats were approximately 26% of those obtained in humans at the recommended clinical dose boosted with ritonavir.

Teratogenic Effects: Category B

Reproduction studies conducted with saquinavir have shown no embryotoxicity or teratogenicity in both rats and rabbits. Because of limited bioavailability of saquinavir in animals and/or dosing limitations, the plasma exposures (AUC values) in the respective species were approximately 29% (using rat) and 21% (using rabbit) of those obtained in humans at the recommended clinical dose boosted with ritonavir. Clinical experience in pregnant women is limited. Saquinavir should be used during pregnancy only if the potential benefit justifies the potential risk to the fetus.

Antiretroviral Pregnancy Registry

To monitor maternal-fetal outcomes of pregnant women exposed to antiretroviral medications, including INVIRASE, an Antiretroviral Pregnancy Registry has been established. Physicians are encouraged to register patients by calling 1-800-258-4263.

Nursing Mothers

The Centers for Disease Control and Prevention recommend that HIV-infected mothers not breast-feed their infants to avoid risking postnatal transmission of HIV. It is not known whether saquinavir is excreted in human milk. Because of both the potential for HIV transmission and the potential for serious adverse reactions in nursing infants, mothers should be instructed not to breast-feed if they are receiving antiretroviral medications, including INVIRASE.

Pediatric Use

Safety and effectiveness of INVIRASE in HIV-infected pediatric patients younger than 16 years of age have not been established.

Geriatric Use

Clinical studies of INVIRASE did not include sufficient numbers of subjects aged 65 and over to determine whether they respond differently from younger subjects. In general, caution should be taken when dosing INVIRASE in elderly patients due to the greater frequency of decreased hepatic, renal or cardiac function, and of concomitant disease or other drug therapy.

ADVERSE REACTIONS

Clinical Trials Experience

Because clinical trials are conducted under widely varying conditions, adverse reaction rates observed in the clinical trials of a drug cannot be directly compared to rates in the clinical trials of another drug and may not reflect the rates observed in clinical practice.

Concomitant Therapy with Ritonavir Adverse Reactions

In combination with ritonavir the recommended dose of INVIRASE is 1000 mg two times daily with ritonavir 100 mg two times daily in combination with other antiretroviral agents. Table 6 lists grade 2, 3 and 4 adverse events that occurred in ≥2% of patients receiving saquinavir soft gel capsules with ritonavir (1000/100 mg bid).

Table 6 Grade 2, 3 and 4 Adverse Events (All Causality [Includes events with unknown relationship to study drug]) Reported in ≥2% of Adult Patients in the MaxCmin 1 Study of saquinavir soft gel capsules in Combination with Ritonavir 1000/100 mg bid
Adverse Events | Saquinavir soft gel capsules 1000 mg plus Ritonavir 100 mg bid (48 weeks) N=148 n (%=n/N)
Endocrine Disorders
Diabetes mellitus/hyperglycemia | 4 (2.7)
Lipodystrophy | 8 (5.4)
Gastrointestinal Disorders
Nausea | 16 (10.8)
Vomiting | 11 (7.4)
Diarrhea | 12 (8.1)
Abdominal Pain | 9 (6.1)
Constipation | 3 (2.0)
General Disorders and Administration Site Conditions
Fatigue | 9 (6.1)
Fever | 5 (3.4)
Musculoskeletal Disorders
Back Pain | 3 (2.0)
Respiratory Disorders
Pneumonia | 8 (5.4)
Bronchitis | 4 (2.7)
Influenza | 4 (2.7)
Sinusitis | 4 (2.7)
Dermatological Disorders
Rash | 5 (3.4)
Pruritus | 5 (3.4)
Dry lips/skin | 3 (2.0)
Eczema | 3 (2.0)

Limited experience is available from three studies investigating the pharmacokinetics of the INVIRASE 500 mg film-coated tablet compared to the INVIRASE 200 mg capsule in healthy volunteers (n=140). In two of these studies saquinavir was boosted with ritonavir; in the other study, saquinavir was administered as single drug. The INVIRASE tablet and the capsule formulations were similarly tolerated. The most common adverse events were gastrointestinal disorders (such as diarrhea). Similar bioavailability was demonstrated and no clinically significant differences in saquinavir exposures were seen. Thus, similar safety profiles are expected between the two INVIRASE formulations.

In a study investigating the drug-drug interaction of rifampin 600 mg/day daily and INVIRASE 1000 mg/ritonavir 100 mg twice daily (ritonavir-boosted INVIRASE) involving 28 healthy volunteers, 11 of 17 healthy volunteers (65%) exposed concomitantly to rifampin and ritonavir-boosted INVIRASE developed severe hepatocellular toxicity which presented as increased hepatic transaminases. In some subjects, transaminases increased up to >20-fold the upper limit of normal and were associated with gastrointestinal symptoms, including abdominal pain, gastritis, nausea, and vomiting. Following discontinuation of all three drugs, clinical symptoms abated and the increased hepatic transaminases normalized (see CONTRAINDICATIONS).

Additional Adverse Reactions Reported with Saquinavir

Additionally, adverse experiences of any intensity, at least remotely related to saquinavir, that were reported from clinical trials using INVIRASE or saquinavir soft gel capsules with or without ritonavir, are listed below by body system:

Body as a Whole: allergic reaction, anorexia, asthenia, chest pain, drug fever, edema, fatigue, fever, intoxication, mucosa damage, parasites external, retrosternal pain, shivering, wasting syndrome, weakness generalized, weight decrease, redistribution/accumulation of body fat (see PRECAUTIONS: Fat Redistribution)

Cardiovascular: cyanosis, heart murmur, heart valve disorder, hypertension, hypotension, peripheral vasoconstriction, syncope, thrombophlebitis, vein distended

Endocrine/Metabolic: appetite decrease, appetite disturbance, dehydration, diabetes mellitus, dry eye syndrome, hypercalcemia, hyperglycemia, hyperkalemia, hypernatremia, hyperphosphatemia, hypertriglyceridemia, hypocalcemia, hypokalemia, hyponatremia, hypophosphatemia, weight increase, xerophthalmia

Gastrointestinal: ascites, abdominal discomfort, buccal mucosa ulceration, cheilitis, colic abdominal, constipation, dyspepsia, dysphagia, esophagitis, eructation, exacerbation of chronic liver disease with grade 4 LFT, feces bloodstained, feces discolored, flatulence, gastralgia, gastritis, gastrointestinal inflammation, intestinal obstruction, gingivitis, glossitis, hemorrhage rectum, hemorrhoids, hepatitis, hepatomegaly, hepatosplenomegaly, hyperbilirubinemia, infectious diarrhea, jaundice, liver enzyme disorder, melena, pain pelvic, painful defecation, pancreatitis, parotid disorder, portal hypertension, right and left upper quadrant abdominal pain, salivary glands disorder, stomach upset, stomatitis, toothache, tooth disorder, vomiting, frequent bowel movements

Hematologic: anemia, bleeding dermal, hemolytic anemia, leukopenia, microhemorrhages, neutropenia, pancytopenia, splenomegaly, thrombocytopenia, lymphadenopathy

Infections and Infestations: abscess, angina tonsillaris, candidiasis, cellulitis, herpes simplex, herpes zoster, infection bacterial, infection mycotic, infection staphylococcal, influenza, moniliasis

Investigations: ALT increase, AST increase, GGT increase, increased alkaline phosphatase, increased creatine phosphokinase, increased gamma GT, isolated increase in transaminase, raised amylase, raised LDH, TSH increase

Musculoskeletal: arthralgia, arthritis, back pain, cramps leg, cramps muscle, creatine phosphokinase increased, musculoskeletal disorders, musculoskeletal pain, myalgia, stiffness, tissue changes, trauma

Neoplasms benign, malignant and unspecified: acute myeloblastic leukemia

Neurological: ataxia, confusion, convulsions, dizziness, dysarthria, dysesthesia, extremity numbness, headache, heart rate disorder, hyperesthesia, hyperreflexia, hyporeflexia, light-headed feeling, mouth dry, myelopolyradiculoneuritis, numbness face, pain facial, paresis, paresthesia, peripheral neuropathy, poliomyelitis, prickly sensation, progressive multifocal leukoencephalopathy, seizures, spasms, intracranial hemorrhage leading to death, tremor, unconsciousness

Psychological: agitation, amnesia, anxiety, anxiety attack, depression, dreaming excessive, euphoria, hallucination, insomnia, intellectual ability reduced, irritability, lethargy, libido disorder, overdose effect, psychic disorder, psychosis, somnolence, speech disorder, suicide attempt

Reproductive System: impotence, prostate enlarged, vaginal discharge

Respiratory: bronchitis, cough, dyspnea, epistaxis, hemoptysis, laryngitis, pharyngitis, pneumonia, pulmonary disease, respiratory disorder, rhinitis, sinusitis, upper respiratory tract infection

Skin and Appendages: acne, alopecia, bullous skin eruption and polyarthritis, chalazion, dermatitis, dermatitis seborrheic, eczema, erythema, folliculitis, furunculosis, hair changes, hot flushes, nail disorder, night sweats, papillomatosis, photosensitivity reaction, pigment changes skin, rash maculopapular, severe cutaneous reaction associated with increased liver function tests, skin disorder, skin nodule, skin ulceration, Stevens-Johnson syndrome, sweating increased, urticaria, verruca, xeroderma

Special Senses: blepharitis, earache, ear pressure, eye irritation, hearing decreased, otitis, taste alteration, tinnitus, visual disturbance

Urinary System: micturition disorder, nephrolithiasis, renal calculus, urinary tract bleeding, urinary tract infection

Postmarketing Experience

Additional adverse events that have been observed during the postmarketing period are similar to those seen in clinical trials with INVIRASE and saquinavir soft gel capsules alone or in combination with ritonavir.

OVERDOSAGE

There is limited experience of overdose with saquinavir.

No acute toxicities or sequelae were noted in 1 patient who ingested 8 grams of INVIRASE as a single dose. The patient was treated with induction of emesis within 2 to 4 hours after ingestion. A second patient ingested 2.4 grams of INVIRASE in combination with 600 mg of ritonavir and experienced pain in the throat that lasted for 6 hours and then resolved. In an exploratory Phase II study of oral dosing with INVIRASE at 7200 mg/day (1200 mg q4h), there were no serious toxicities reported through the first 25 weeks of treatment.

Treatment of overdose with saquinavir should consist of general supportive measures including monitoring of vital signs and ECG and observations of the patient's clinical status. Since saquinavir is highly protein bound, dialysis is unlikely to be beneficial in significant removal of the active substance.

DOSAGE AND ADMINISTRATION

INVIRASE must be used in combination with ritonavir, because it significantly inhibits saquinavir's metabolism to provide increased plasma saquinavir levels.

Adults (Over the Age of 16 Years)

- INVIRASE 1000-mg twice daily (5 × 200-mg capsules or 2 × 500-mg tablets) in combination with ritonavir 100-mg twice daily.
- Ritonavir should be taken at the same time as INVIRASE.
- INVIRASE and ritonavir should be taken within 2 hours after a meal.

Concomitant Therapy: INVIRASE with Lopinavir/Ritonavir

When administered with lopinavir/ritonavir 400/100 mg twice daily, the appropriate dose of INVIRASE is 1000 mg twice daily (with no additional ritonavir).

Monitoring of Patients

Clinical chemistry tests, viral load, and CD4 count should be performed prior to initiating INVIRASE therapy and at appropriate intervals thereafter.

Dose Adjustment for Combination Therapy with INVIRASE

For serious toxicities that may be associated with INVIRASE, the drug should be interrupted. INVIRASE at doses less than 1000 mg with 100 mg ritonavir twice daily are not recommended since lower doses have not shown antiviral activity. For recipients of combination therapy with INVIRASE and ritonavir, dose adjustments may be necessary. These adjustments should be based on the known toxicity profile of the individual agent and the pharmacokinetic interaction between saquinavir and the coadministered drug (see PRECAUTIONS: Drug Interactions). Physicians should refer to the complete product information for these drugs for comprehensive dose adjustment recommendations and drug-associated adverse reactions of nucleoside analogues.

HOW SUPPLIED

INVIRASE 200-mg capsules are light brown and green opaque capsules with ROCHE and 0245 imprinted on the capsule .

INVIRASE 500-mg film-coated tablets are light orange to greyish- or brownish-orange, oval cylindrical, biconvex tablets with ROCHE and SQV 500 imprinted on the tablet face.

They are supplied by State of Florida DOH Central Pharmacy as follows:

NDC | Strength | Quantity/Form | Color | Source Prod. Code
53808-0674-1 | 500 mg | 30 Tablets in a Blister Pack | light orange to greyish-or brownish-orange | 0004-0244

STORAGE AND HANDLING

The capsules and tablets should be stored at 25°C (77°F); excursions permitted to 15° to 30°C (59° to 86°F) [see USP Controlled Room Temperature] in tightly closed bottles.

Capsules Manufactured by:
F. Hoffmann-La Roche Ltd., Basel, Switzerland

Tablets Manufactured by:
Roche Farma, S.A., Leganes, Spain

Distributed by:
Roche Laboratories Inc.
340 Kingsland Street
Nutley, New Jersey 07110-1199

Copyright © 1998-2010 by Roche Laboratories Inc. All rights reserved.

This Product was Repackaged By:

State of Florida DOH Central Pharmacy
104-2 Hamilton Park Drive
Tallahassee, FL 32304
United States

Patient Information About INVIRASE (in-ver-ase)

INVIRASE®
(saquinavir mesylate)
CAPSULES and TABLETS
Generic Name: Saquinavir mesylate (sa-KWIN-a-veer mes-il-late)

ALERT: Find out about medicines that should NOT be taken with INVIRASE.

Please read this product information carefully before you start taking INVIRASE and each time you renew your prescription. There may be new information. Reading this information can help you take this medicine correctly. However, it is not a substitute for your doctor's advice about the safety and benefits of INVIRASE. You should talk to your doctor about INVIRASE as part of your long-term treatment plan for HIV before you start taking your medication and ask any questions you may have at regular checkups. Remember, you should remain under a doctor's care when using INVIRASE and should not change or stop your therapy without talking to your doctor first.

What is INVIRASE?

INVIRASE belongs to a class of anti-HIV medicines called protease (PRO-tee-ase) inhibitors. INVIRASE Capsules and Tablets in combination with other anti-HIV drugs are used for the treatment of HIV, the virus that causes AIDS (acquired immunodeficiency syndrome).

How does INVIRASE work?

INVIRASE fights HIV as it grows inside cells by blocking an enzyme (protease) that HIV needs to reproduce.

Who should not take INVIRASE?

Anyone who has had a severe allergic reaction (e.g. trouble breathing or severe rash) to INVIRASE or any of the ingredients in the capsule or tablet should not take it. The use of INVIRASE in patients under 16 years of age, over 65 years of age, or patients with severe liver problems has not been fully investigated.

How should INVIRASE/NORVIR® (ritonavir) be taken?

- The recommended dosage of INVIRASE in combination with NORVIR (ritonavir) is INVIRASE 5 capsules or 2 tablets twice a day taken with 1 capsule of NORVIR twice a day. Your doctor may change the dose of other medications you may be taking for other illnesses.
- INVIRASE must be taken along with NORVIR (ritonavir).
- INVIRASE must be taken with meals or up to 2 hours after a meal—but it is easiest to remember if you take it with your meals. When INVIRASE is taken without food, the amount of INVIRASE in the blood is lower and may not fight HIV as well.
- When taking INVIRASE and other anti-HIV medicines, it is very important to follow the directions exactly and take your medication every day. If you skip doses—or take less than the prescribed dose—the medicine will not work as well, and your disease could get worse.
  - If you miss a dose, you should take the next dose as soon as possible. However, do not double the dose.

What results have been seen with INVIRASE?

INVIRASE with NORVIR has been shown to reduce the amount of virus in the blood ("viral load") and increase CD4 (T) cells when taken with other HIV therapy.

What are the side effects of INVIRASE?

People treated with INVIRASE in combination with NORVIR may have side effects. The majority of these have been described as mild. In clinical studies of patients who received saquinavir in combination with NORVIR and other HIV drugs, the side effects seen most often were: body fat change (5.4%), nausea (10.8%), vomiting (7.4%), diarrhea (8.1%), stomach pain (6.1%), tiredness (6.1%), and pneumonia (5.4%).

Diabetes (new onset or worsening) and increased blood sugar levels have been reported with the use of protease inhibitors. In addition, increased bleeding in patients with hemophilia has also been associated with these drugs.

When INVIRASE is taken with NORVIR, some patients may experience large increases in triglyceride and lipid levels. The long-term chance of getting complications such as heart attack and stroke due to increases in triglyceride and cholesterol levels caused by protease inhibitors is not known at this time.

Changes in body fat have been seen in some patients taking anti-HIV medications. These changes may include increased amount of fat in the upper back and neck ("buffalo hump"), breasts, and around the trunk. Loss of fat from the legs and arms may also happen. The cause and long-term health effects of these conditions are not known at this time.

These are not the only side effects that can occur with INVIRASE. Your doctor can discuss with you a more complete list of side effects and laboratory abnormalities that may accompany this medication.

If any side effects or unusual symptoms do occur, contact your doctor immediately. Do not stop or decrease your dose on your own. Lowering the dose may make INVIRASE less effective in fighting HIV.

Are there other medications that I should not take with INVIRASE/NORVIR (ritonavir)?

There are some drugs that should not be taken with INVIRASE/NORVIR. Before starting therapy with INVIRASE/NORVIR, be sure to tell your doctor all of the medicines—prescription medications, as well as over-the-counter drugs and nutritional supplements—that you are now taking or plan to take.

Medicines you should not take with INVIRASE/NORVIR
Drug Class | Drugs Within Class Not to Be Taken with INVIRASE/NORVIR (ritonavir)
Antiarrhythmics | PACERONE® (amiodarone), TAMBOCOR® (flecainide), RHYTHMOL® (propafenone), bepridil, quinidine
Antimigraines | Ergot medications (e.g. WIGRAINE® and CAFERGOT®)
GI motility agents | PROPULSID® (cisapride) [No longer sold in the US.]
Sedatives, hypnotics | VERSED® (orally administered midazolam), Halcion® (triazolam)
Antimycobacterial agents | Rifampin
Neuroleptics | ORAP® (Pimozide)
HMG-CoA Reductase Inhibitors | MEVACOR® ALTOPREV®, ADVICOR® (lovastatin), ZOCOR®, VYTORIN®, SIMCOR® (simvastatin)

INVIRASE causes increased blood levels of some of these compounds. This can lead to serious or life-threatening reactions such as irregular heartbeat or prolonged sedation.

The following medicines may increase blood levels and side effects of INVIRASE when taken with INVIRASE/NORVIR:

- REYATAZ® (atazanavir, used for HIV infection)
- PRILOSEC® (omeprazole, for treatment of gastrointestinal conditions such as ulcers or GERD)
- BIAXIN® (clarithromycin, for treatment of infections)
- CRIXIVAN® (indinavir, used for HIV infection)

INVIRASE/NORVIR may not work as well when taken together with the following medicines, herbal products, or dietary supplements:

- SUSTIVA® (efavirenz, used for HIV infection)
- VIRAMUNE® (nevirapine, used for HIV infection)
- APTIVUS® ([tipranavir]/NORVIR [ritonavir] used for HIV infection)
- Anticonvulsants such as CARBATROL® (carbamazepine), phenobarbital, and DILANTIN® (phenytoin)
- MYCOBUTIN® (rifabutin, an antimycobacterial agent)
- Corticosteroids such as dexamethasone
- Garlic capsules, an herbal product sold as a dietary supplement
- St. John's wort (Hypericum perforatum) or products containing St. John's wort, an herbal product sold as a dietary supplement

Your healthcare provider may need to monitor your therapy more closely if you take INVIRASE/NORVIR with the following medicines:

- CIALIS® (tadalafil), LEVITRA® (vardenafil), or VIAGRA® (sildenafil citrate) used for erectile dysfunction. INVIRASE may increase the chances of serious side effects that can happen with CIALIS, LEVITRA, or VIAGRA
- COUMADIN® (warfarin) (a blood thinner)
- Antidepressants such as DESYREL® (trazodone), ELAVIL® (amitriptyline), or TOFRANIL® (imipramine)
- Benzodiazepines used as sedatives or sleeping pills such as XANAX® (alprazolam), TRANXENE® (clorazepate), VALIUM® (diazepam), and DALMANE® (flurazepam)
- LIPITOR® (atorvastatin) and CRESTOR® (rosuvastatin) used for lowering cholesterol
- Calcium channel blockers used for treatment of high blood pressure or heart disease, such as diltiazem (also known as CARDIZEM®, CARTIA XT®, DILACOR XR®, DILTZAC® TAZTIA XT®, TIAZAC®), PLENDIL® (felodipine), PROCARDIA® (nifedipine), CARDENE® (nicardipine), NIMOTOP® (nimodipine), verapamil-containing medications (such as CALAN®, VERELAN®), amlodipine-containing medications (such as CADUET®, NORVASC®), SULAR® (nisoldipine), and DYNACIRC® (isradipine)
- NIZORAL® (ketoconazole) and SPORANOX® (itraconazole) used to treat fungal infections
- Medicines to prevent organ transplant rejection: SANDIMMUNE® (cyclosporine), NEORAL® (cyclosporine), RAPAMUNE® (sirolimus), or PROGRAF® (tacrolimus)
- FLONASE®, FLOVENT®, ADVAIR® (fluticasone propionate), given by nose or inhaled to treat allergic symptoms or asthma
- LANOXIN® (digoxin) used to treat heart rhythm problems or other heart conditions
- Oral contraceptives containing ethinyl estradiol used for preventing pregnancy
- Methadone used for the treatment of opioid addiction

Does INVIRASE cure HIV/AIDS?

INVIRASE does not cure AIDS, and it does not prevent you from getting other illnesses that result from advanced HIV infection. In addition, INVIRASE has not been shown to reduce the risk that you may transmit HIV to others through sexual contact or infected blood. You must continue to follow all of your doctor's recommendations for managing your illness.

What else should I discuss with my doctor?

Inform your doctor:

- If you are pregnant or become pregnant while taking INVIRASE. The effects of INVIRASE on pregnant women or unborn babies are not yet fully known. In addition, experts advise against breast-feeding if you are HIV positive, to reduce the risk of passing the virus to your baby.
- If you are taking anti-HIV medications. Your doctor may want to change one or more of your anti-HIV drugs in order to achieve the best results when you start treatment with INVIRASE.
- If you have diabetes or a family history of diabetes, or if you have hemophilia, hepatitis or other liver disease, your doctor should decide if INVIRASE is right for you.
- If you have ever taken FORTOVASE, discuss with your doctor whether INVIRASE is right for you.

How is INVIRASE supplied?

INVIRASE is available as light brown and green capsules in a 200-mg strength. INVIRASE comes in bottles of 270 capsules.

INVIRASE is also available as light orange to greyish- or brownish-orange tablets in a 500-mg strength. INVIRASE comes in bottles of 120 tablets.

How should I store INVIRASE?

INVIRASE capsules and tablets should be stored at room temperature. The bottles should be kept tightly closed.

INVIRASE has been prescribed specifically for you, and only for a particular condition. Do not use it for anything else. Do not give it to anyone else. If you think you have taken more than your prescribed dose, seek medical attention.

Keep this medication and all other medications out of the reach of children. Do not keep medicine that is out of date or that you no longer need. Be sure that if you throw any medicine away, it is out of the reach of children.

This provides only a brief summary of product information about INVIRASE. If you have any questions about INVIRASE or HIV, talk to your doctor.

The brands listed are trademarks of their respective owners and are not trademarks of Roche Laboratories, Inc. The makers of these brands are not affiliated with and do not endorse Roche Laboratories, Inc. or its products.

If you have any questions about INVIRASE, call toll free at 1-800-910-4687.

Distributed by:
Roche Pharmaceuticals
Roche Laboratories Inc.
340 Kingsland Street
Nutley, New Jersey 07110-1199

Copyright © 1999-2010 by Roche Laboratories Inc. All rights reserved.

This Product was Repackaged By:

State of Florida DOH Central Pharmacy
104-2 Hamilton Park Drive
Tallahassee, FL 32304
United States

Representative sample of labeling (see the HOW SUPPLIED section for complete listing):

PRINCIPAL DISPLAY PANEL - 500 mg Tablets Bottle

NDC 53808-0674-1

Invirase®
(saquinavir mesylate) Tablets

500 mg

Each tablet contains
saquinavir mesylate equivalent to
500 mg saquinavir (free base).

30 tablets
Rx only

ALERT: Find out about medicines that
should NOT be taken with INVIRASE.

Roche